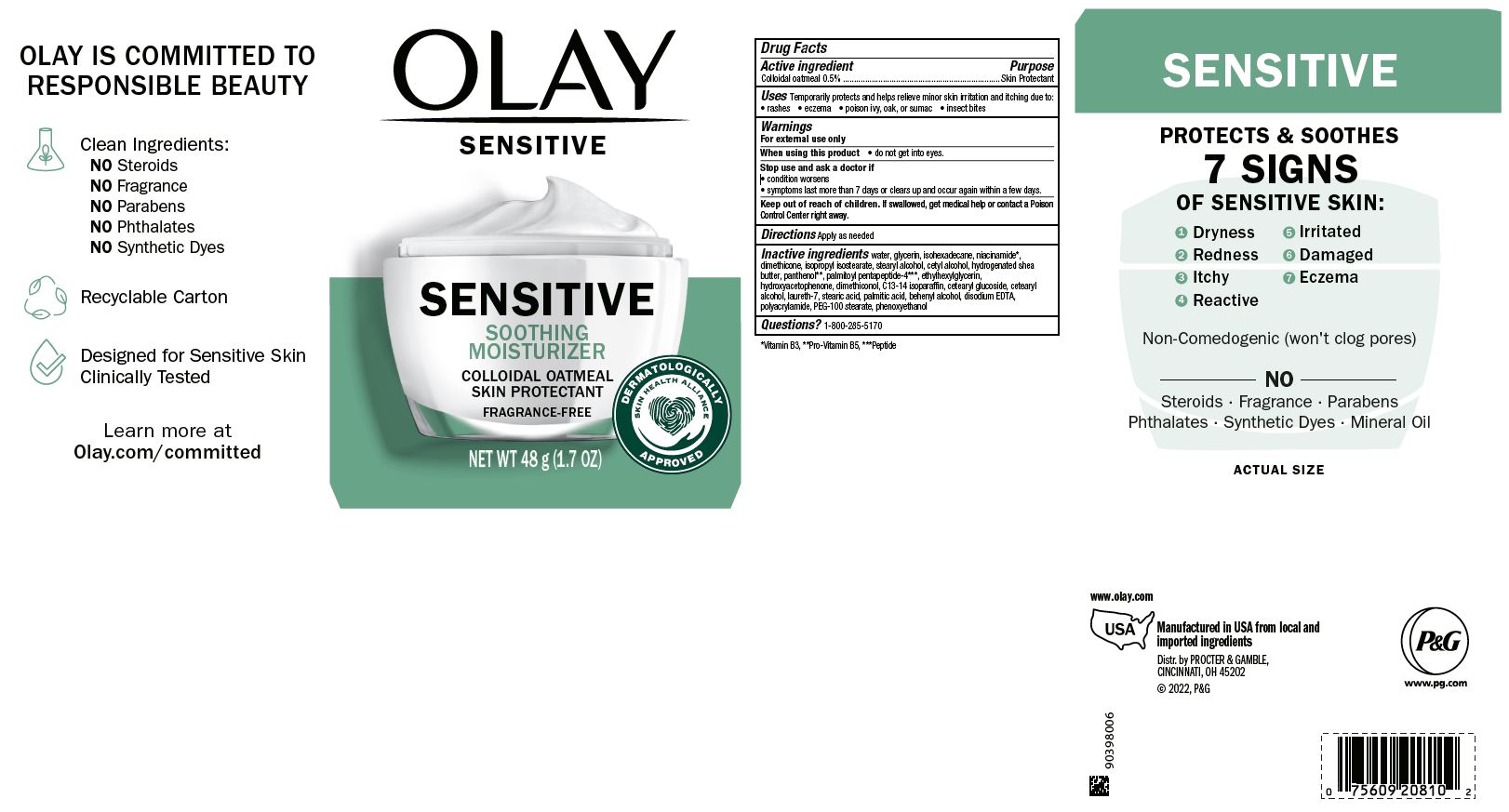 DRUG LABEL: Olay Sensitive Soothing Moisturizer Skin Protectant Fragrance-Free
NDC: 69423-700 | Form: CREAM
Manufacturer: The Procter & Gamble Manufacturing Company
Category: otc | Type: HUMAN OTC DRUG LABEL
Date: 20250304

ACTIVE INGREDIENTS: OATMEAL 0.5 g/100 g
INACTIVE INGREDIENTS: PALMITIC ACID; ETHYLHEXYLGLYCERIN; GLYCERIN; DIMETHICONOL (50000 CST); CETEARYL GLUCOSIDE; ISOHEXADECANE; SHEA BUTTER; PALMITOYL PENTAPEPTIDE-4; LAURETH-7; NIACINAMIDE; ISOPROPYL ISOSTEARATE; CETYL ALCOHOL; HYDROXYACETOPHENONE; POLYACRYLAMIDE (1300000 MW); DIMETHICONE; EDETATE DISODIUM; PHENOXYETHANOL; C13-14 ISOPARAFFIN; WATER; STEARIC ACID; STEARYL ALCOHOL; PANTHENOL; CETOSTEARYL ALCOHOL; DOCOSANOL; PEG-100 STEARATE

Olay Sensitive Soothing Moisturizer Colloidal Oatmeal Skin Protectant Fragrance-Free

Drug Facts

Active ingredients

Colloidal Oatmeal 0.5%

Purpose

Skin Protectant

Uses

Temporarily protects and helps relieve minor skin irritation and itching due to:

rashes eczema poison ivy, oak or sumac insect bites

Warnings

For external use only.

WHEN USING

Do not get into eyes.

Stop use and ask a doctor if condition worsens, symptoms last more than 7 days or clear up and occur again within a few days

Keep out of reach of children. If swallowed, get medical help or contact a Poison Control Center right away.

Directions

Apply as needed

INACTIVE INGREDIENT

Water, glycerin, isohexadecane, niacinamide, dimethicone, isopropyl isostearate, stearyl alcohol, cetyl alcohol, hydrogenated shea butter, panthenol, palmitoyl pentapeptide-4, ethylhexylglycerin, hydroxyacetophenone, dimethiconol, C13-14 isoparaffin, cetearyl Glucoside, cetearyl alcohol, laureth-7, stearic acid, palmitic acid, behenyl alcohol, disodium EDTA, polyacrylamide, PEG-100 stearate, phenoxyethanol

Questions:

1-800-285-5170

Manufactured in USA from local and

Imported Ingredients

Distr. by PROCTER & GAMBLE,

CINCINNATI, OH 45202

www.olay.com

PRINCIPAL DISPLAY PANEL - 1.70 oz (48 g)

OLAY

SENSITIVE

SENSITIVE

SOOTHING

MOISTURIZER

Colloidal Oatmeal

Skin Protectant

FRAGRANCE-FREE

Net Wt. 48 g (1.7 oz)